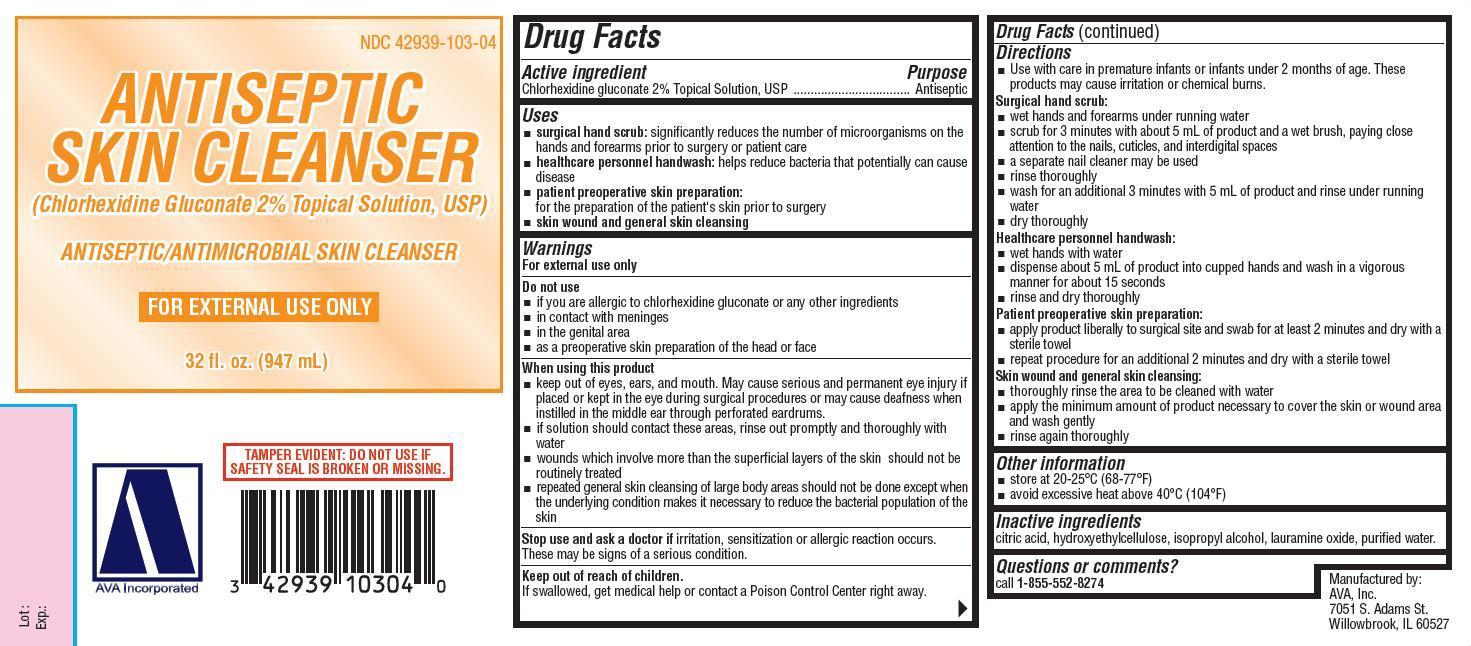 DRUG LABEL: ANTISEPTIC SKIN CLEANSER
NDC: 42939-103 | Form: SOLUTION
Manufacturer: AVA, Inc.
Category: otc | Type: HUMAN OTC DRUG LABEL
Date: 20121216

ACTIVE INGREDIENTS: CHLORHEXIDINE GLUCONATE 2 g/100 mL
INACTIVE INGREDIENTS: ANHYDROUS CITRIC ACID; HYDROXYETHYL CELLULOSE (140 CPS AT 5%); ISOPROPYL ALCOHOL; LAURAMINE OXIDE; WATER

Antiseptic Skin Cleanser
(Chlorhexidine Gluconate 2% Topical Solution, USP)

Drug Facts

Active ingredient

Chlorhexidine gluconate 2% Topical Solution, USP

Purposes

surgical hand scrub
healthcare personnel handwash
patient preoperative skin preparation
skin wound and general skin cleansing

Uses

- surgical hand scrub: significantly reduces the number of microorganisms on the hands and forearms prior to surgery or patient care
- healthcare personnel handwash: helps reduce bacteria that potentially can cause disease
- patient preoperative skin preparation: for the preparation of the patient's skin prior to surgery
- skin wound and general skin cleansing

Warnings

For external use only

Do not use

- if you are allergic to chlorhexidine gluconate or any other ingredients
- in contact with meninges
- in the genital area
- as a preoperative skin preparation of the head or face

When using this product

- keep out of eyes, ears, and mouth. May cause serious and permanent eye injury if placed or kept in the eye during surgical procedures or may cause deafness when instilled in the middle ear through perforated eardrums
- if solution should contact these areas, rinse out promptly and thoroughly with water
- wounds which involve more than the superficial layers of the skin should not be routinely treated
- repeated general skin cleansing of large body areas should not be done except when the underlying condition makes it necessary to reduce the bacterial population of the skin

Stop use and ask a doctor if irritation, sensitization or allergic reaction occurs. These may be signs of a serious condition.

Keep out of reach of children.

If swallowed, get medical help or contact a Poison Control Center right away.

Directions Use with care in premature infants or infants under 2 months of age. These products may cause irritation or chemical burns.

Surgical hand scrub

- wet hands and forearms under running water
- scrub for 3 minutes with about 5 ml of product and a wet brush, paying close attention to the nails, cuticles, and interdigital spaces
- a separate nail cleaner may be used
- rinse thoroughly
- wash for an additional 3 minutes with 5 ml of product and rinse under running water
- dry thoroughly

Healthcare personnel handwash

- wet hands with water
- dispense about 5 ml of product into cupped hands and wash in a vigorous manner for 15 seconds
- rinse and dry thoroughly

Patient preoperative skin preparation

- apply product liberally to surgical site and swab for at least 2 minutes and dry with a sterile towel
- repeat procedure for an additional 2 minutes and dry with a sterile towel

Skin wound and general skin cleansing

- thoroughly rinse the area to be cleaned with water
- apply the minimum amount of product necessary to cover the skin or wound area and wash gently
- rinse again thoroughly

Other information

- store at 20-25°C (68-77°F)
- avoid excessive heat above 40°C (104°F)

Inactive ingredients

citric acid, hydroxyethylcellulose, isopropyl alcohol, lauramine oxide, purified water.

Questions or comments?

Call 1-855-552-8274

Manufactured by:
AVA, Inc.
7051 S. Adams St.
Willowbrook, IL 60527

PRINCIPAL DISPLAY PANEL - 947 mL Bottle Label

NDC 42939-103-04

ANTISEPTIC SKIN CLEANSER

(Chlorhexidine Gluconate 2% Topical Solution, USP)

ANTISEPTIC/ANTIMICROBIAL SKIN CLEANSER

FOR EXTERNAL USE ONLY

32 fl.oz. (974 mL)

TAMPER EVIDENT: DO NOT USE IF SAFETY SEAL IS BROKEN OR MISSING

AVA Incorporated

Lot:

Exp: